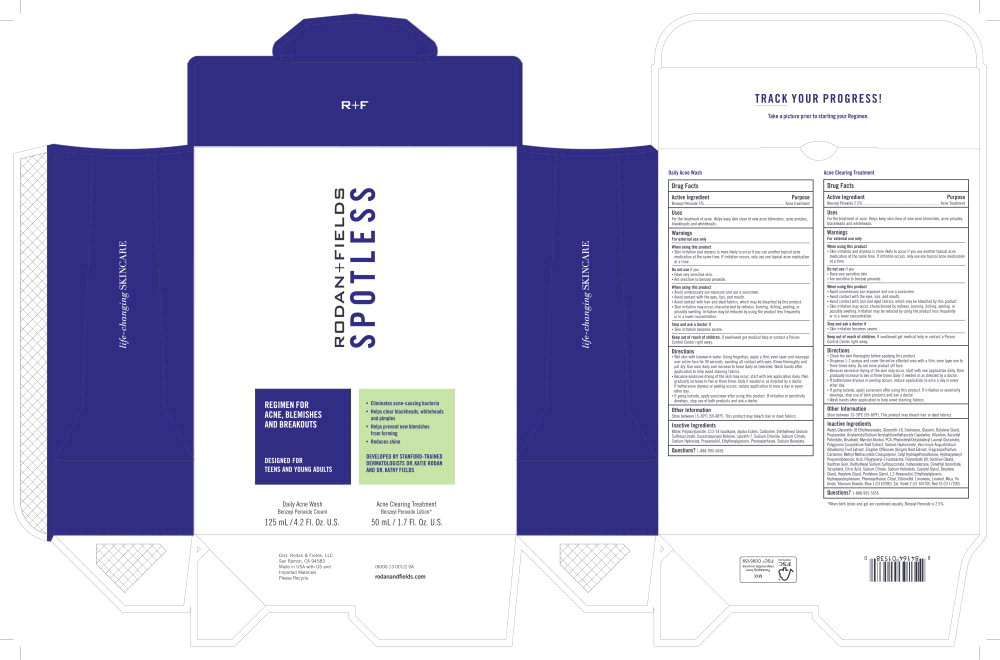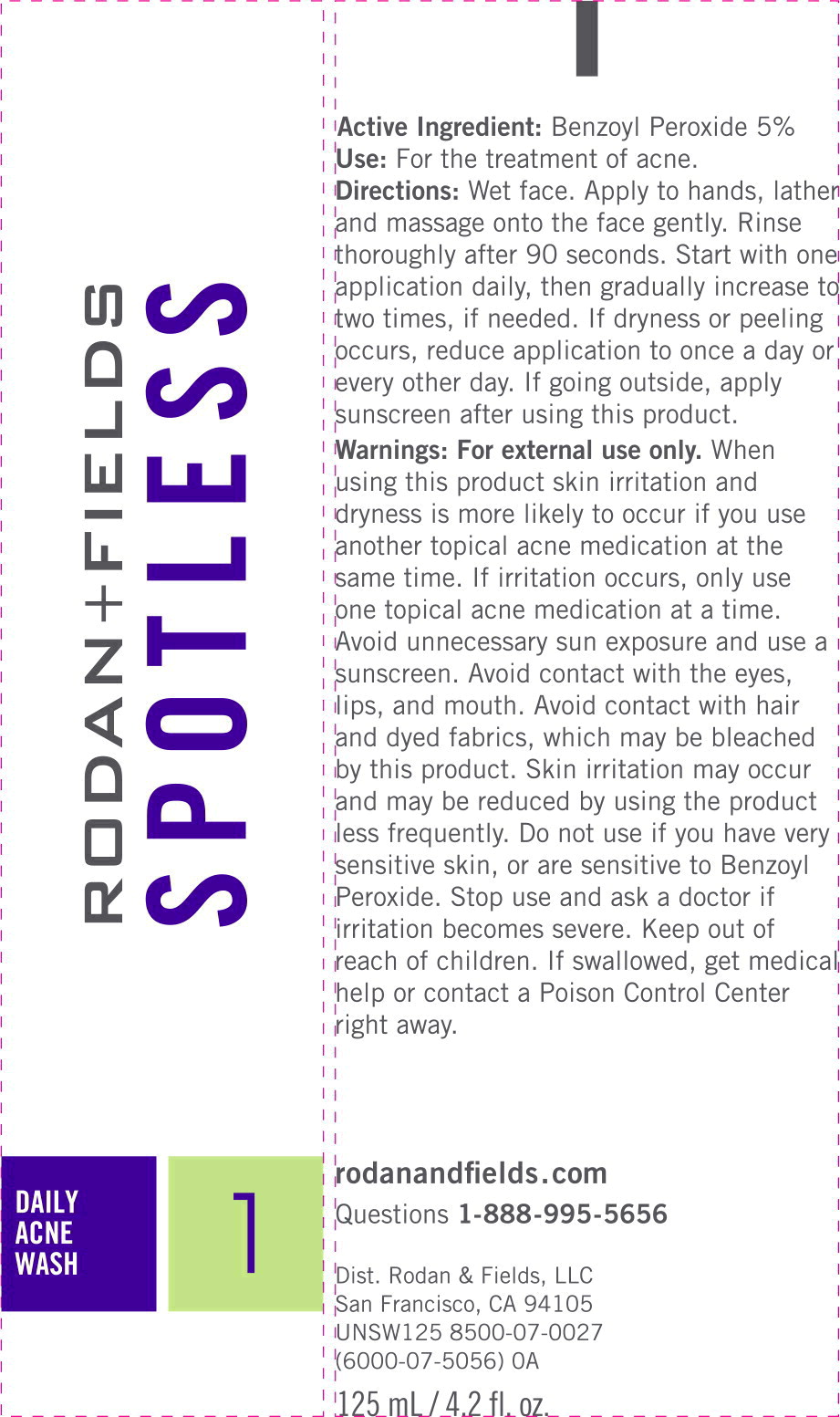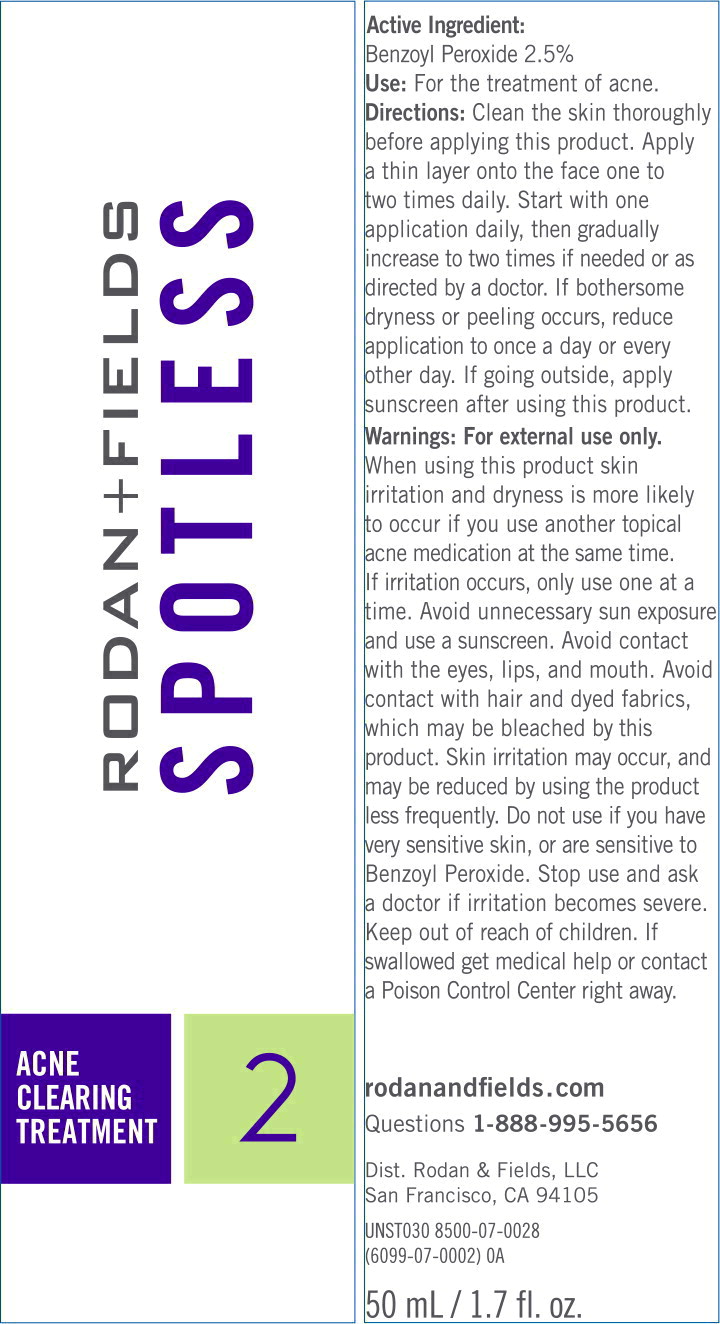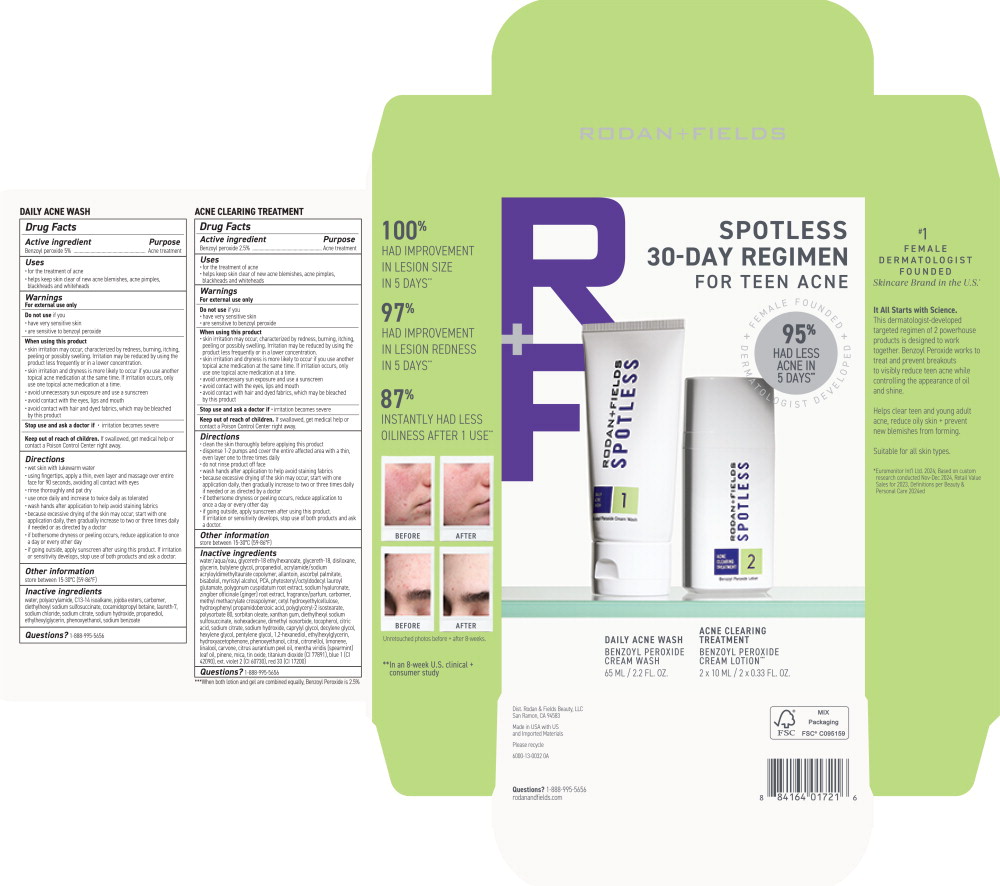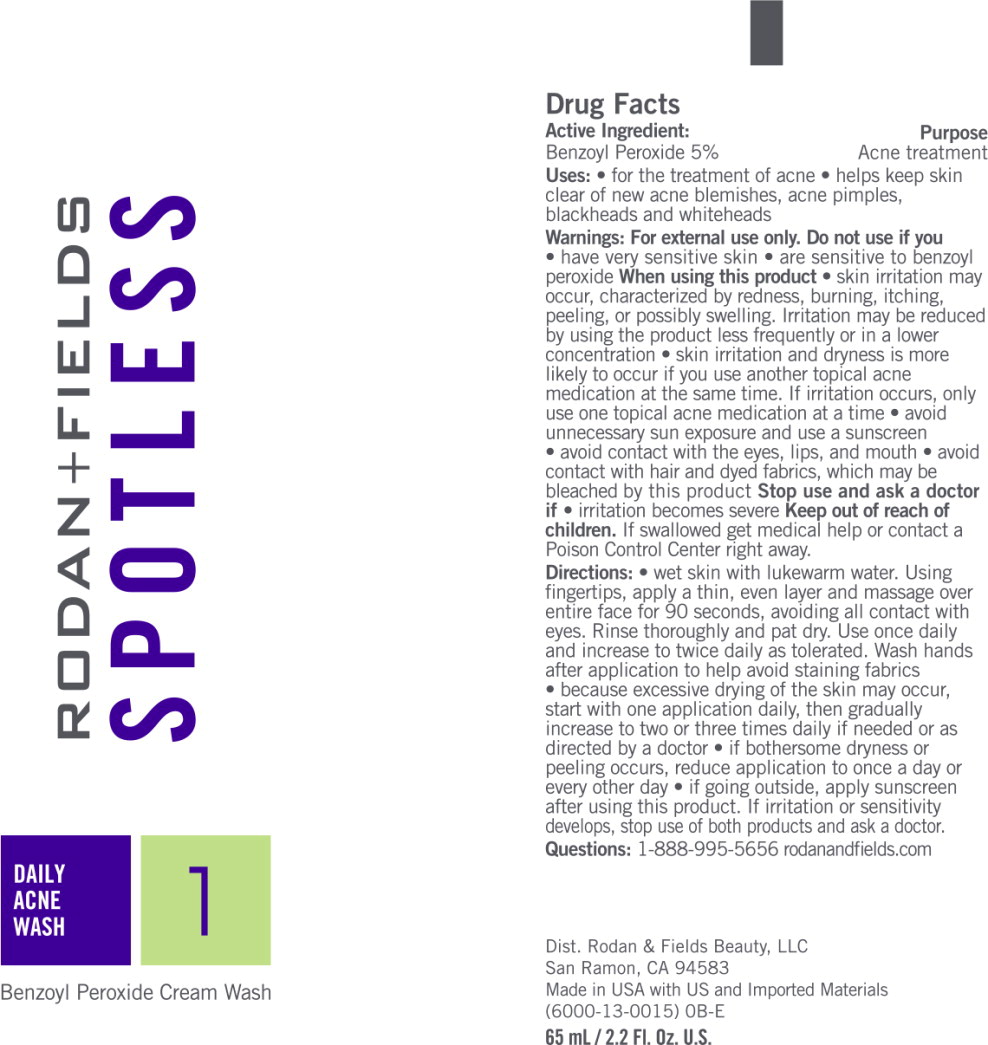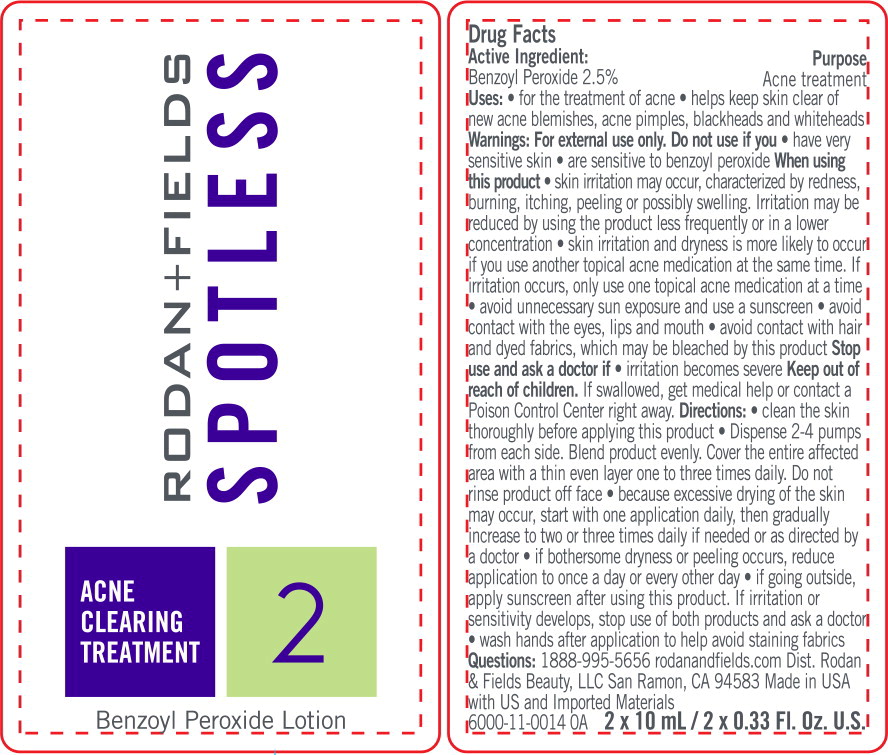 DRUG LABEL: SPOTLESS REGIMEN FOR ACNE, BLEMISHES AND BREAKOUTS
NDC: 14222-1600 | Form: KIT | Route: TOPICAL
Manufacturer: Rodan & Fields
Category: otc | Type: HUMAN OTC DRUG LABEL
Date: 20260204

ACTIVE INGREDIENTS: BENZOYL PEROXIDE 0.05 g/1 mL; BENZOYL PEROXIDE 0.025 g/1 mL
INACTIVE INGREDIENTS: WATER; POLYACRYLAMIDE (10000 MW); C13-14 ISOPARAFFIN; CARBOXYPOLYMETHYLENE; COCAMIDOPROPYL BETAINE; DOCUSATE SODIUM; ETHYLHEXYLGLYCERIN; HYDROGENATED JOJOBA OIL, RANDOMIZED; LAURETH-7; PHENOXYETHANOL; PROPANEDIOL; SODIUM BENZOATE; SODIUM CHLORIDE; SODIUM CITRATE, UNSPECIFIED FORM; SODIUM HYDROXIDE; WATER; GLYCERETH-18 ETHYLHEXANOATE; GLYCERETH-18; HEXAMETHYLDISILOXANE; GLYCERIN; BUTYLENE GLYCOL; PROPANEDIOL; ACRYLAMIDE/SODIUM ACRYLOYLDIMETHYLTAURATE COPOLYMER (120000 MPA.S AT 1%); ALLANTOIN; ASCORBYL PALMITATE; LEVOMENOL; MYRISTYL ALCOHOL; PIDOLIC ACID; PHYTOSTERYL/OCTYLDODECYL LAUROYL GLUTAMATE; REYNOUTRIA JAPONICA ROOT; HYALURONATE SODIUM; GINGER; POLYACRYLIC ACID (800000 MW); METHYL METHACRYLATE/GLYCOL DIMETHACRYLATE CROSSPOLYMER; CETYL HYDROXYETHYLCELLULOSE (350000 MW); HYDROXYPHENYL PROPAMIDOBENZOIC ACID; POLYGLYCERYL-2 ISOSTEARATE; POLYSORBATE 80; SORBITAN MONOOLEATE; XANTHAN GUM; DOCUSATE SODIUM; ISOHEXADECANE; DIMETHYL ISOSORBIDE; TOCOPHEROL; CITRIC ACID MONOHYDRATE; SODIUM CITRATE, UNSPECIFIED FORM; SODIUM HYDROXIDE; CAPRYLYL GLYCOL; DECYLENE GLYCOL; HEXYLENE GLYCOL; PENTYLENE GLYCOL; 1,2-HEXANEDIOL; ETHYLHEXYLGLYCERIN; HYDROXYACETOPHENONE; PHENOXYETHANOL; CITRAL; .BETA.-CITRONELLOL, (R)-; LIMONENE, (+/-)-; LINALOOL, (+/-)-; CARVONE, (+/-)-; BITTER ORANGE OIL; SPEARMINT OIL; PINENE; MICA; STANNIC OXIDE; TITANIUM DIOXIDE; FD&C BLUE NO. 1; Ext. D&C VIOLET NO. 2; D&C RED NO. 33

DAILY ACNE WASH

Drug Facts

Active ingredient

Benzoyl peroxide 5%

Purpose

Acne treatment

Uses

- for the treatment of acne
- helps keep skin clear of new acne blemishes, acne pimples, blackheads and whiteheads

Warnings

For external use only

Do not use if you

- have very sensitive skin
- are sensitive to benzoyl peroxide

When using this product

- skin irritation may occur, characterized by redness, burning, itching, peeling or possibly swelling. Irritation may be reduced by using the product less frequently or in a lower concentration.
- skin irritation and dryness is more likely to occur if you use another topical acne medication at the same time. If irritation occurs, only use one topical acne medication at a time.
- avoid unnecessary sun exposure and use a sunscreen
- avoid contact with the eyes, lips and mouth
- avoid contact with hair and dyed fabrics, which may be bleached by this product

Stop use and ask a doctor if

- irritation becomes severe

Keep out of reach of children. If swallowed, get medical help or contact a Poison Control Center right away.

Directions

- wet skin with lukewarm water
- using fingertips, apply a thin, even layer and massage over entire face for 90 seconds, avoiding all contact with eyes
- rinse thoroughly and pat dry
- use once daily and increase to twice daily as tolerated
- wash hands after application to help avoid staining fabrics
- because excessive drying of the skin may occur, start with one application daily, then gradually increase to two or three times daily if needed or as directed by a doctor
- if bothersome dryness or peeling occurs, reduce application to once a day or every other day
- if going outside, apply sunscreen after using this product. If irritation or sensitivity develops, stop use of both products and ask a doctor.

Other information

store between 15-30°C (59-86°F)

Inactive ingredients

water, polyacrylamide, C13-14 isoalkane, jojoba esters, carbomer, diethylhexyl sodium sulfosuccinate, cocamidopropyl betaine, laureth-7, sodium chloride, sodium citrate, sodium hydroxide, propanediol, ethylhexylglycerin, phenoxyethanol, sodium benzoate

Questions?

1-888-995-5656

ACNE CLEARING TREATMENT

Drug Facts

Active ingredient

Benzoyl peroxide 2.5%

Purpose

Acne treatment

Uses

- for the treatment of acne
- helps keep skin clear of new acne blemishes, acne pimples, blackheads and whiteheads

Warnings

For external use only

Do not use if you

- have very sensitive skin
- are sensitive to benzoyl peroxide

When using this product

- skin irritation may occur, characterized by redness, burning, itching, peeling or possibly swelling. Irritation may be reduced by using the product less frequently or in a lower concentration.
- skin irritation and dryness is more likely to occur if you use another topical acne medication at the same time. If irritation occurs, only use one topical acne medication at a time.
- avoid unnecessary sun exposure and use a sunscreen
- avoid contact with the eyes, lips and mouth
- avoid contact with hair and dyed fabrics, which may be bleached by this product

Stop use and ask a doctor if

- irritation becomes severe

Keep out of reach of children. If swallowed, get medical help or contact a Poison Control Center right away.

Directions

- clean the skin thoroughly before applying this product
- dispense 1-2 pumps and cover the entire affected area with a thin, even layer one to three times daily
- do not rinse product off face
- wash hands after application to help avoid staining fabrics
- because excessive drying of the skin may occur, start with one application daily, then gradually increase to two or three times daily if needed or as directed by a doctor
- if bothersome dryness or peeling occurs, reduce application to once a day or every other day
- if going outside, apply sunscreen after using this product.

If irritation or sensitivity develops, stop use of both products and ask a doctor.

Other information

store between 15-30°C (59-86°F)

Inactive ingredients

water/aqua/eau, glycereth-18 ethylhexanoate, glycereth-18, disiloxane, glycerin, butylene glycol, propanediol, acrylamide/sodium acryloyldimethyltaurate copolymer, allantoin, ascorbyl palmitate, bisabolol, myristyl alcohol, PCA, phytosteryl/octyldodecyl lauroyl glutamate, polygonum cuspidatum root extract, sodium hyaluronate, zingiber officinale (ginger) root extract, fragrance/parfum, carbomer, methyl methacrylate crosspolymer, cetyl hydroxyethylcellulose, hydroxyphenyl propamidobenzoic acid, polyglyceryl-2 isostearate, polysorbate 80, sorbitan oleate, xanthan gum, diethylhexyl sodium sulfosuccinate, isohexadecane, dimethyl isosorbide, tocopherol, citric acid, sodium citrate, sodium hydroxide, caprylyl glycol, decylene glycol, hexylene glycol, pentylene glycol, 1,2-hexanediol, ethylhexylglycerin, hydroxyacetophenone, phenoxyethanol, citral, citronellol, limonene, linalool, carvone, citrus aurantium peel oil, mentha viridis (spearmint) leaf oil, pinene, mica, tin oxide, titanium dioxide (CI 77891), blue 1 (CI 42090), ext. violet 2 (CI 60730), red 33 (CI 17200)

Questions?

1-888-995-5656

Principal Display Panel - Kit Label

RODAN+FIELDS

SPOTLESS

REGIMEN FOR
ACNE, BLEMISHES
AND BREAKOUTS

DESIGNED FOR
TEENS AND YOUNG ADULTS

- Eliminates acne-causing bacteria
- Helps clear blackheads, whiteheads
  and pimples
- Helps prevent new blemishes
  from forming
- Reduces shine

DEVELOPED BY STANFORD-TRAINED
DERMATOLOGISTS DR.KATIE RODAN
AND DR.KATHY FIELDS

Daily Acne Wash

Benzoyl Peroxide Cream

125 mL/4.2 Fl. Oz. U.S.

Acne Clearing Treatment

Benzoyl Peroxide Lotion*

50 mL/1.7 Fl. Oz. U.S.

Principal Display Panel - Daily Acne Wash Tube Label

RODAN+FIELDS
SPOTLESS

DAILY
ACNE
WASH

1

Principal Display Panel - Acne Clearing Treatment Tube Label

RODAN+FIELDS
SPOTLESS

ACNE
CLEARING
TREATMENT

2

Principal Display Panel - 30-DAY KIT Carton Label

RODAN+FIELDS

SPOTLESS
30-DAY REGIMEN
FOR TEEN ACNE

FEMALE FOUNDED + DERMATOLOGIST DEVELOPED

95%
HAD LESS
ACNE IN
5 DAYS**

DAILY ACNE WASH
BENZOYL PEROXIDE
CREAM WASH
65 ML / 2.2 FL. OZ.

ACNE CLEARING
TREATMENT
BENZOYL PEROXIDE
CREAM LOTION***

2 x 10 ML / 2 x 0.33 FL. OZ.

Principal Display Panel - 65 mL Tube Label

RODAN+FIELDS
SPOTLESS

DAILY
ACNE
WASH
1

Benzoyl Peroxide Cream Wash

Principal Display Panel - 20 mL Tube Label

RODAN+FIELDS
SPOTLESS

ACNE
CLEARING
TREATMENT
2

Benzoyl Peroxide Lotion